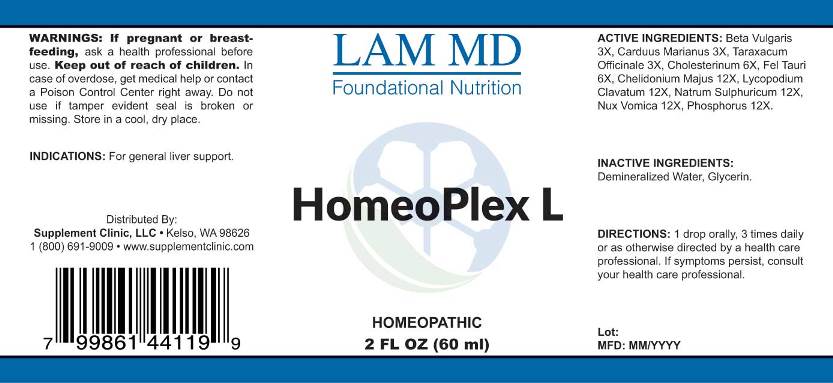 DRUG LABEL: Homeoplex L
NDC: 71781-0006 | Form: LIQUID
Manufacturer: Supplement Clinic, LLC.
Category: homeopathic | Type: HUMAN OTC DRUG LABEL
Date: 20171101

ACTIVE INGREDIENTS: BETA VULGARIS 3 [hp_X]/1 mL; MILK THISTLE 3 [hp_X]/1 mL; TARAXACUM OFFICINALE 3 [hp_X]/1 mL; CHOLESTEROL 6 [hp_X]/1 mL; BOS TAURUS BILE 6 [hp_X]/1 mL; CHELIDONIUM MAJUS 12 [hp_X]/1 mL; LYCOPODIUM CLAVATUM SPORE 12 [hp_X]/1 mL; SODIUM SULFATE 12 [hp_X]/1 mL; STRYCHNOS NUX-VOMICA SEED 12 [hp_X]/1 mL; PHOSPHORUS 12 [hp_X]/1 mL
INACTIVE INGREDIENTS: WATER; GLYCERIN

Drug Facts:

ACTIVE INGREDIENTS:

Beta Vulgaris 3X, Carduus Marianus 3X, Taraxacum Officinale 3X, Cholesterinum 6X, Fel Tauri 6X, Chelidonium Majus 12X, Lycopodium Clavatum 12X, Natrum Sulphuricum 12X, Nux Vomica 12X, Phosphorus 12X.

INDICATIONS:

For general liver support.

WARNINGS:

If pregnant or breast-feeding, ask a health professional before use.
Keep out of reach of children. In case of overdose, get medical help or contact a Poison Control Center right away.
Do not use if tamper evident seal is broken or missing.
Store in cool, dry place.

Keep out of reach of children. In case of overdose, get medical help or contact a Poison Control Center right away.

DIRECTIONS:

1 drop orally, 3 times daily or as otherwise directed by a health care professional. If symptoms persist, consult your health care professional.

INDICATIONS:

For general liver support.

INACTIVE INGREDIENTS:

Demineralized Water, Glycerin

QUESTIONS:

Distributed By:
Supplement Clinic, LLC. • Kelso, WA 98626
1(800)691-9009 • www.supplementclinic.com

PACKAGE LABEL DISPLAY:

LAM MD
Foundational Nutrition

HomeoPlex L

HOMEOPATHIC
2 FL OZ (60 ml)